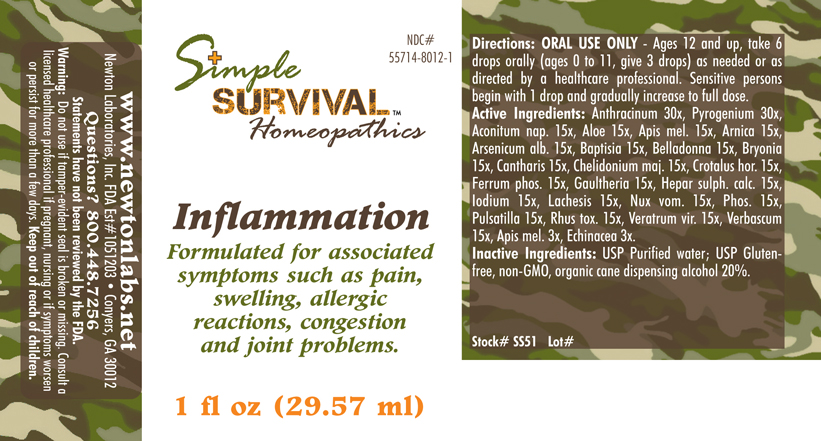 DRUG LABEL: Inflammation 
NDC: 55714-8012 | Form: LIQUID
Manufacturer: Newton Laboratories, Inc.
Category: homeopathic | Type: HUMAN OTC DRUG LABEL
Date: 20140415

ACTIVE INGREDIENTS: Bacillus Anthracis Immunoserum Rabbit 30 [hp_X]/1 mL; Rancid Beef 30 [hp_X]/1 mL; Aconitum Napellus 15 [hp_X]/1 mL; Aloe 15 [hp_X]/1 mL; Apis Mellifera 15 [hp_X]/1 mL; Arnica Montana 15 [hp_X]/1 mL; Arsenic Trioxide 15 [hp_X]/1 mL; Baptisia Tinctoria Root 15 [hp_X]/1 mL; Atropa Belladonna 15 [hp_X]/1 mL; Bryonia Alba Root 15 [hp_X]/1 mL; Lytta Vesicatoria 15 [hp_X]/1 mL; Chelidonium Majus 15 [hp_X]/1 mL; Crotalus Horridus Horridus Venom 15 [hp_X]/1 mL; Ferrosoferric Phosphate 15 [hp_X]/1 mL; Gaultheria Procumbens Top 15 [hp_X]/1 mL; Calcium Sulfide 15 [hp_X]/1 mL; Iodine 15 [hp_X]/1 mL; Lachesis Muta Venom 15 [hp_X]/1 mL; Strychnos Nux-vomica Seed 15 [hp_X]/1 mL; Phosphorus 15 [hp_X]/1 mL; Pulsatilla Vulgaris 15 [hp_X]/1 mL; Toxicodendron Pubescens Leaf 15 [hp_X]/1 mL; Veratrum Viride Root 15 [hp_X]/1 mL; Verbascum Thapsus 15 [hp_X]/1 mL; Echinacea, Unspecified 3 [hp_X]/1 mL
INACTIVE INGREDIENTS: Alcohol

Inflammation

INDICATIONS & USAGE SECTION

Inflammation Formulated for associated symptoms such as pain, swelling, allergic reactions, congestion and joint problems.

DOSAGE & ADMINISTRATION SECTION

Directions: ORAL USE ONLY - Ages 12 and up, take 6 drops orally (ages 0 to 11, give 3 drops) as needed or as directed by a healthcare professional. Sensitive persons begin with 1 drop and gradually increase to full dose.

OTC - ACTIVE INGREDIENT SECTION

Anthracinum 30x, Pyrogenium 30x, Aconitum nap. 15x, Aloe 15x, Apis mel. 15x, Arnica 15x, Arsenicum alb. 15x, Baptisia 15x, Belladonna 15x, Bryonia 15x, Cantharis 15x, Chelidonium maj. 15x, Crotalus hor. 15x, Ferrum phos. 15x, Gaultheria 15x, Hepar sulph. calc. 15x, Iodium 15x, Lachesis 15x, Nux vom. 15x, Phos. 15x, Pulsatilla 15x, Rhus tox. 15x, Veratrum vir. 15x, Verbascum 15x, Apis mel. 3x, Echinacea 3x.

OTC - PURPOSE SECTION

Formulated for associated symptoms such as pain, swelling, allergic reactions, congestion and joint problems.

INACTIVE INGREDIENT SECTION

Inactive Ingredients: USP Purified Water; USP Gluten-free, non-GMO, organic cane dispensing alcohol 20%.

QUESTIONS SECTION

www.newtonlabs.net Newton Laboratories, Inc. FDA Est # 1051203 - Conyers, GA 30012
Questions? 1.800.448.7256

WARNINGS SECTION

Warning: Do not use if tamper - evident seal is broken or missing. Consult a licensed healthcare professional if pregnant, nursing or if symptoms worsen or persist for more than a few days. Keep out of reach of children.

OTC - PREGNANCY OR BREAST FEEDING SECTION

Consult a licensed healthcare professional if pregnant, nursing or if symptoms worsen or persist for more than a few days.

OTC - KEEP OUT OF REACH OF CHILDREN SECTION

Keep out of reach of children